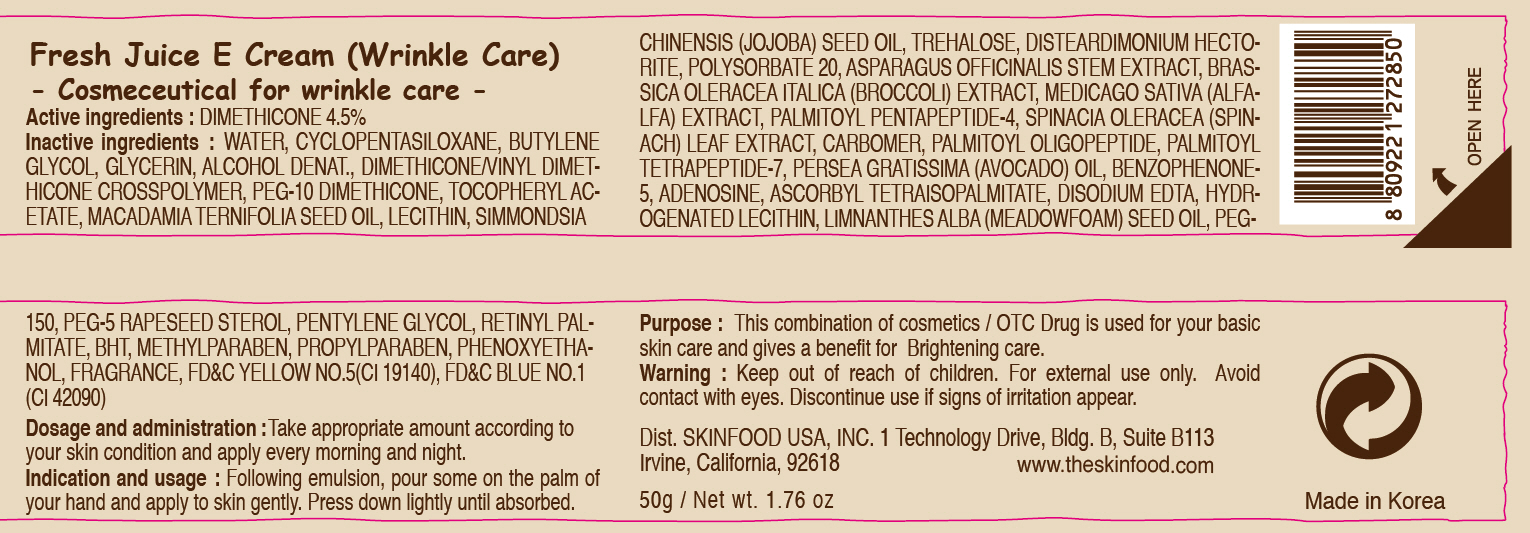 DRUG LABEL: FRESH JUICE E
NDC: 76214-025 | Form: CREAM
Manufacturer: SKINFOOD CO., LTD.
Category: otc | Type: HUMAN OTC DRUG LABEL
Date: 20110923

ACTIVE INGREDIENTS: DIMETHICONE 2.25 g/50 g
INACTIVE INGREDIENTS: WATER; CYCLOMETHICONE 5; BUTYLENE GLYCOL; GLYCERIN; MACADAMIA OIL; LECITHIN, SOYBEAN; TREHALOSE; POLYSORBATE 20; PHENOXYETHANOL; ASPARAGUS; BROCCOLI; ALFALFA SEED; SPINACH; METHYLPARABEN; PALMITOYL PENTAPEPTIDE-4; PALMITOYL OLIGOPEPTIDE; PALMITOYL TETRAPEPTIDE-7; AVOCADO OIL; PROPYLPARABEN; BUTYLATED HYDROXYTOLUENE; ADENOSINE; EDETATE DISODIUM; HYDROGENATED SOYBEAN LECITHIN; MEADOWFOAM SEED OIL; POLYETHYLENE GLYCOL 7000; PENTYLENE GLYCOL; VITAMIN A PALMITATE

Drug Facts

Active ingredient: DIMETHICONE 4.5%

Inactive ingredients:
WATER, CYCLOPENTASILOXANE, BUTYLENE GLYCOL, GLYCERIN, ALCOHOL DENAT., DIMETHICONE/VINYL DIMETHICONE CROSSPOLYMER, PEG-10 DIMETHICONE, TOCOPHERYL ACETATE, MACADAMIA TERNIFOLIA SEED OIL, LECITHIN, SIMMONDSIA CHINENSIS (JOJOBA) SEED OIL, TREHALOSE, DISTEARDIMONIUM HECTORITE, POLYSORBATE 20, ASPARAGUS OFFICINALIS STEM EXTRACT, BRASSICA OLERACEA ITALICA (BROCCOLI) EXTRACT, MEDICAGO SATIVA (ALFALFA) EXTRACT, PALMITOYL PENTAPEPTIDE-4, SPINACIA OLERACEA (SPINACH) LEAF EXTRACT, CARBOMER, PALMITOYL OLIGOPEPTIDE, PALMITOYL TETRAPEPTIDE-7, PERSEA GRATISSIMA (AVOCADO) OIL, BENZOPHENONE-5, ADENOSINE, ASCORBYL TETRAISOPALMITATE, DISODIUM EDTA, HYDROGENATED LECITHIN, LIMNANTHES ALBA (MEADOWFOAM) SEED OIL, PEG-150, PEG-5 RAPESEED STEROL, PENTYLENE GLYCOL, RETINYL PALMITATE, BHT, METHYLPARABEN, PROPYLPARABEN, PHENOXYETHANOL, FRAGRANCE

PURPOSE

Purpose: This combination of cosmetics / OTC Drug is used for your basic skin care and gives a benefit for Brightening care.

Warnings:
For external use only.
Avoid contact with eyes.
Discontinue use if signs of irritation appear.

Keep out of reach of children:
Keep out of reach of children.

Indication and usage:
Following emulsion, pour some on the palm of your hand and apply to skin gently.
Press down lightly until absorbed.

Dosage and administration:
Take appropriate amount according to your skin condition and apply every morning and night.